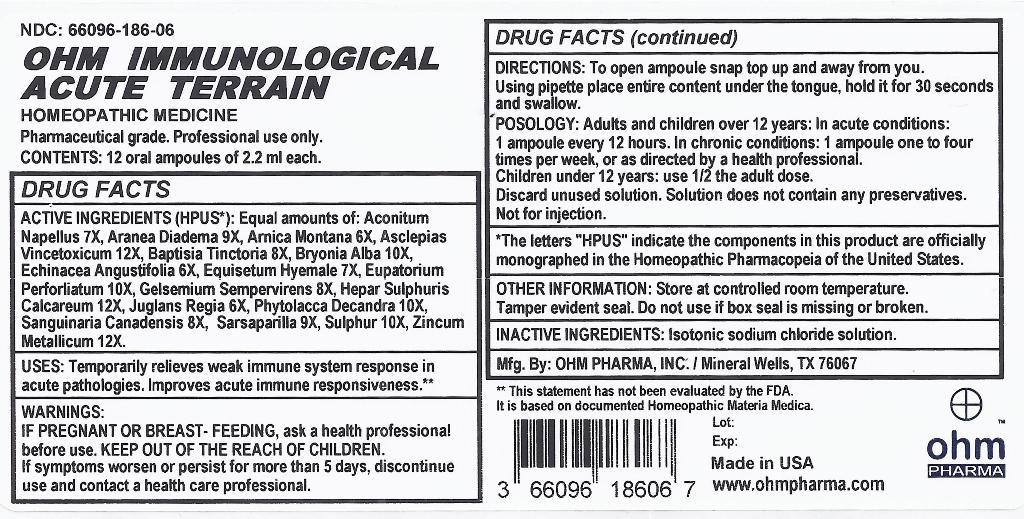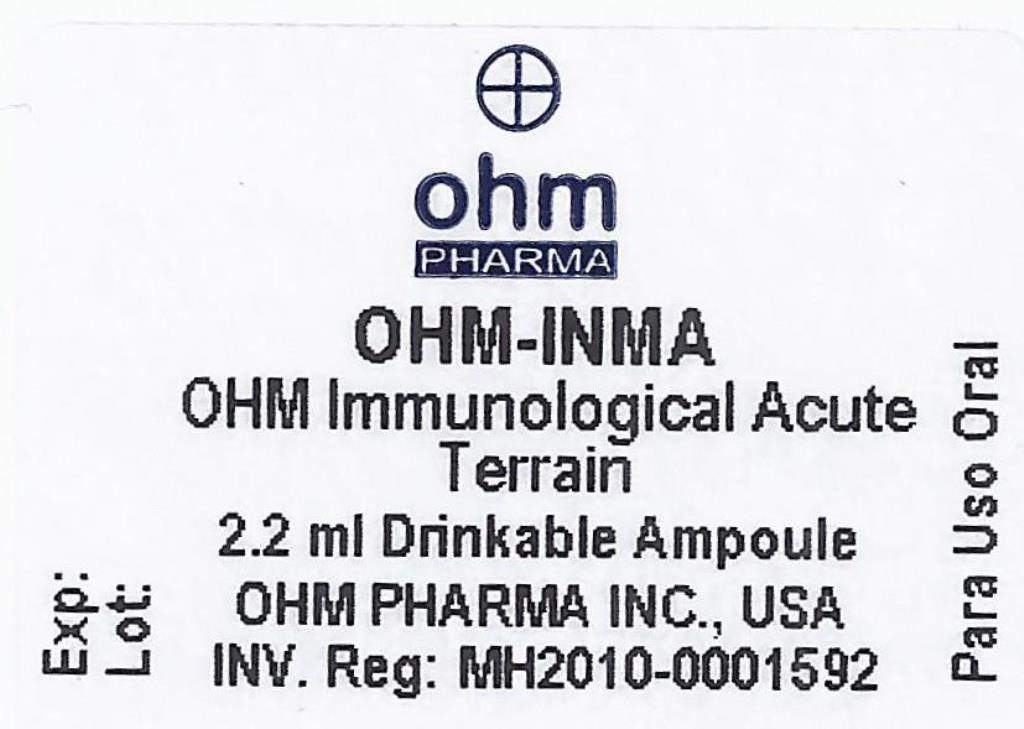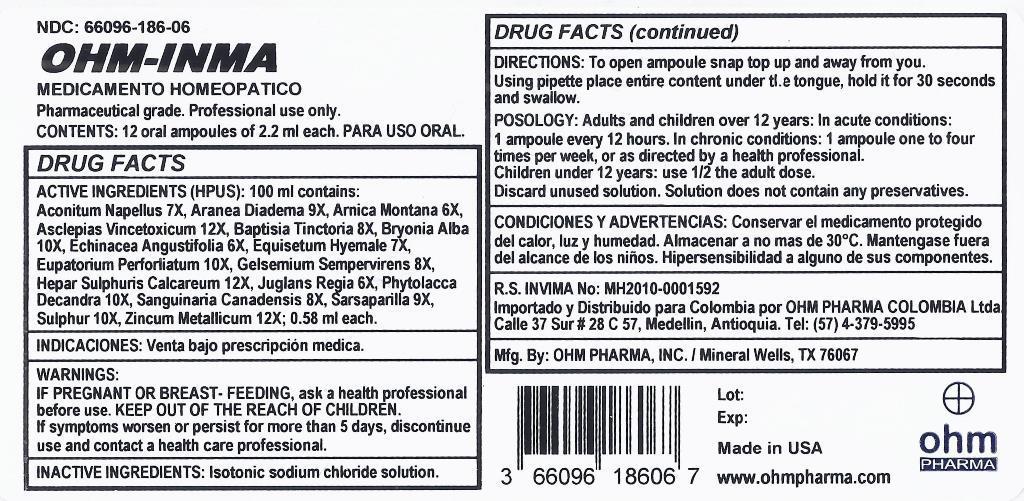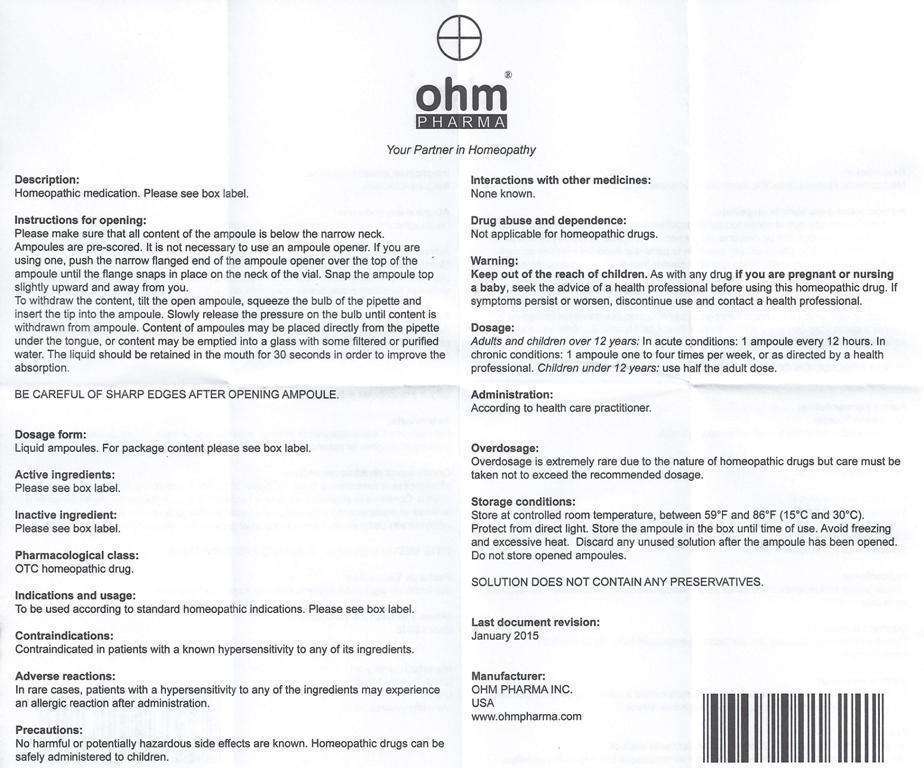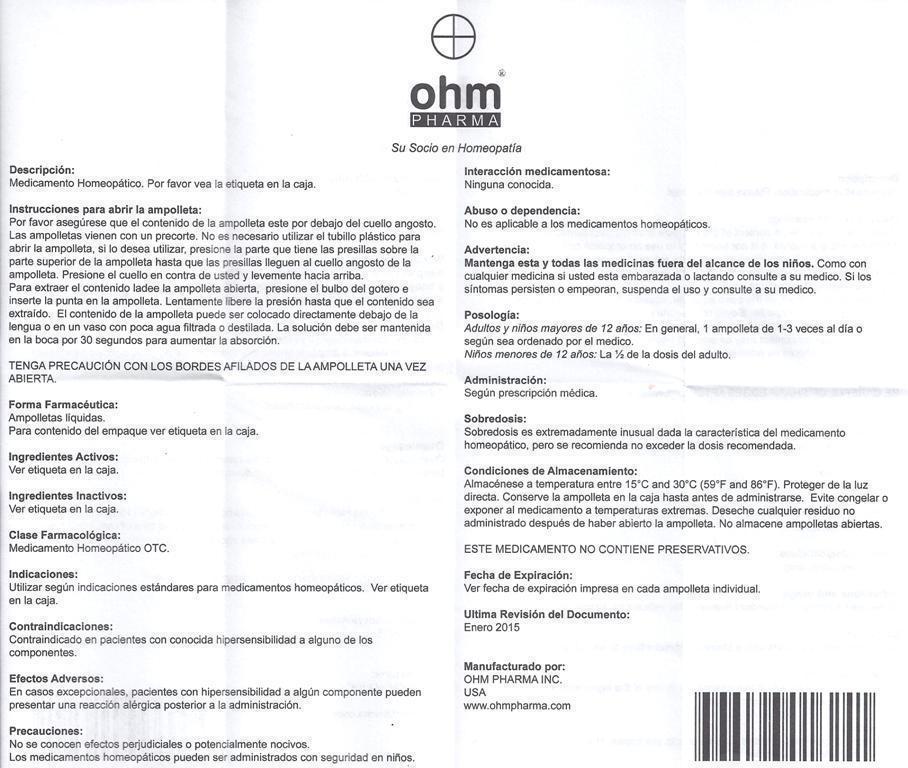 DRUG LABEL: OHM IMMUNOLOGICAL ACUTE TERRAIN
NDC: 66096-186 | Form: LIQUID
Manufacturer: OHM PHARMA INC.
Category: homeopathic | Type: HUMAN OTC DRUG LABEL
Date: 20160111

ACTIVE INGREDIENTS: ACONITUM NAPELLUS 7 [hp_X]/1 mL; ARANEUS DIADEMATUS 9 [hp_X]/1 mL; ARNICA MONTANA 6 [hp_X]/1 mL; CYNANCHUM VINCETOXICUM ROOT 12 [hp_X]/1 mL; BAPTISIA TINCTORIA 8 [hp_X]/1 mL; BRYONIA ALBA ROOT 10 [hp_X]/1 mL; ECHINACEA ANGUSTIFOLIA 6 [hp_X]/1 mL; EQUISETUM HYEMALE 7 [hp_X]/1 mL; EUPATORIUM PERFOLIATUM FLOWERING TOP 10 [hp_X]/1 mL; GELSEMIUM SEMPERVIRENS ROOT 8 [hp_X]/1 mL; CALCIUM SULFIDE 12 [hp_X]/1 mL; JUGLANS REGIA LEAF 6 [hp_X]/1 mL; PHYTOLACCA AMERICANA ROOT 10 [hp_X]/1 mL; SANGUINARIA CANADENSIS ROOT 8 [hp_X]/1 mL; SMILAX REGELII ROOT 9 [hp_X]/1 mL; SULFUR 10 [hp_X]/1 mL; ZINC 12 [hp_X]/1 mL
INACTIVE INGREDIENTS: SODIUM CHLORIDE

OHM IMMUNOLOGICAL ACUTE TERRAIN

ACTIVE INGREDIENT

ACTIVE INGREDIENTS (HPUS*): Equal amounts of: Aconitum Napellus 7X, Aranea Diadema 9X, Arnica Montana 6X, Asclepias Vincetoxicum 12X, Baptisia Tinctoria 8X, Bryonia Alba 10X, Echinacea Angustifolia 6X, Equisetum Hyemale 7X, Eupatorium Perforiatum 10X, Gelsemium Sempervirens 8X, Hepar Sulphuris Calcareum 12X, Juglans Regia 6X, Phytolacca Decandra 10X, Sanguinaria Canadensis 8X, Sarsaparilla 9X, Sulphur 10X, Zincum Metallicum 12X.

ACTIVE INGREDIENT

*The letters "HPUS" indicate the components in this product are officially monographed in the Homeopathic Pharmacopeia of the United States.

INDICATIONS AND USAGE

USES: Temporarily relieves weak immune system response in acute pathologies. Improves acute immune responsiveness.**

**This statement has not been evaluated by the FDA.
It is based on documented Homeopathic Materia Medica.

WARNINGS:

IF PREGNANT OR BREAST-FEEDING, ask a health professional before use. If symptoms worsen or persist for more than 5 days, discontinue use and contact a health care professional.

KEEP OUT OF THE REACH OF CHILDREN.

DOSAGE AND ADMINISTRATION

DIRECTIONS: To open ampoule snap top up and away from you. Using pipette place entire content under the tongue, hold it for 30 seconds and swallow.

POSOLOGY: Adults and children over 12 years: In acute conditions: 1 ampoule every 12 hours. In chronic conditions: 1 ampoule one to four times per week, or as directed by a health professional.

Children under 12 years use 1/2 the adult dose.

Discard unused solution. Solution does not contain any preservatives.

Not for injection.

OTHER INFORMATION: Store at controlled room temperature. Tamper evident seal. Do not use if box seal is missing or broken.

INACTIVE INGREDIENTS: Isotonic sodium chloride solution.

QUESTIONS

Mfg. By: OHM PHARMA, INC. / Mineral Wells, TX 76067

Made in USA

www.ohmpharma.com

PURPOSE

Weak immune system response relief

PACKAGE LABEL

NDC: 66096-186-06

OHM IMMUNOLOGICAL ACUTE TERRAIN

HOMEOPATHIC MEDICINE

Pharmaceutical Grade. Professional use only.

CONTENTS: 12 oral ampoules of 2.2 ml each.